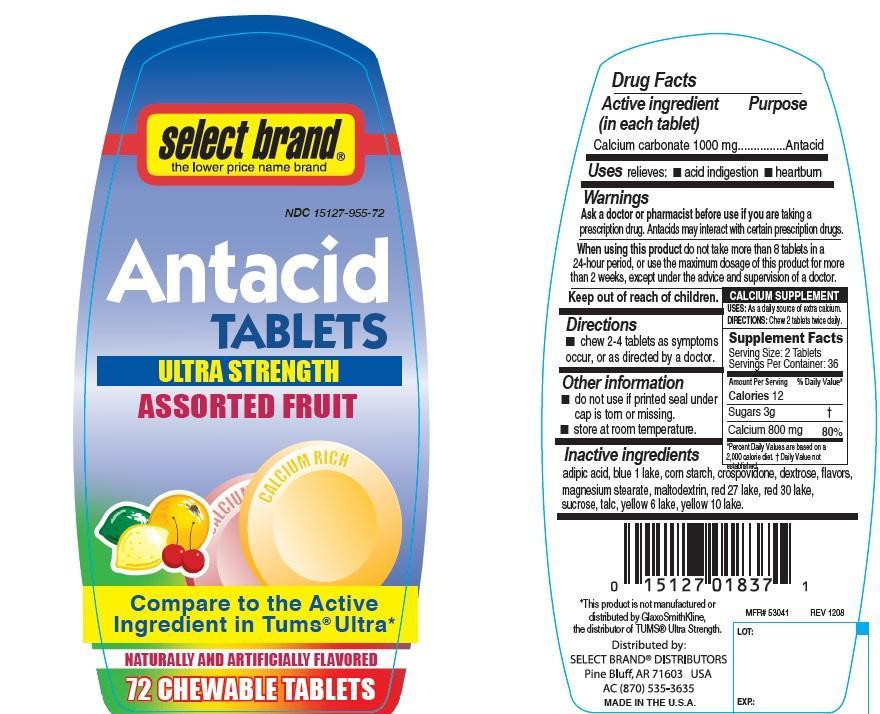 DRUG LABEL: antacid
NDC: 15127-955 | Form: TABLET, CHEWABLE
Manufacturer: Select Brand
Category: otc | Type: HUMAN OTC DRUG LABEL
Date: 20141002

ACTIVE INGREDIENTS: CALCIUM CARBONATE 1000 mg/1 1
INACTIVE INGREDIENTS: ADIPIC ACID; STARCH, CORN; CROSPOVIDONE; D&C RED NO. 27; D&C RED NO. 30; D&C YELLOW NO. 10; DEXTROSE; FD&C BLUE NO. 1; FD&C YELLOW NO. 6; MAGNESIUM STEARATE; MALTODEXTRIN; SUCROSE; TALC

Select Brand Ultra Strength Assorted Fruit Antacid Tablets

Active ingredient (in each tablet)

Calcium carbonate 1000 mg

Purpose

Antacid

Uses

relieves

- acid indigestion
- heartburn

Warnings

Ask a doctor or pharmacist before use if you are

taking a prescription drug. Antacids may interact with certain prescription drugs.

When using this product

do not take more than 8 tablets in a 24-hour period, or use the maximum dosage of this product for more than 2 weeks, except under the advice and supervision of a doctor.

Keep out of reach of children.

Directions

- chew 2-4 tablets as symptoms occur, or as directed by a doctor.

Other information

- do not use if printed seal under cap is torn or missing.
- store at room temperature

Inactive ingredients

adipic acid, corn starch, crospovidone, red 27 lake, red 30 lake, yellow 10 lake, dextrose, blue 1 lake, yellow 6 lake, flavors, magnesium stearate, maltodextrin, sucrose, talc.

Principal Display Panel

Select Brand

Compare to the active ingredient in TUMS® ULTRA

Antacid Tablets

Ultra Strength

Assorted Fruit

Naturally and Artificially Flavored

72 CHEWABLE TABLETS